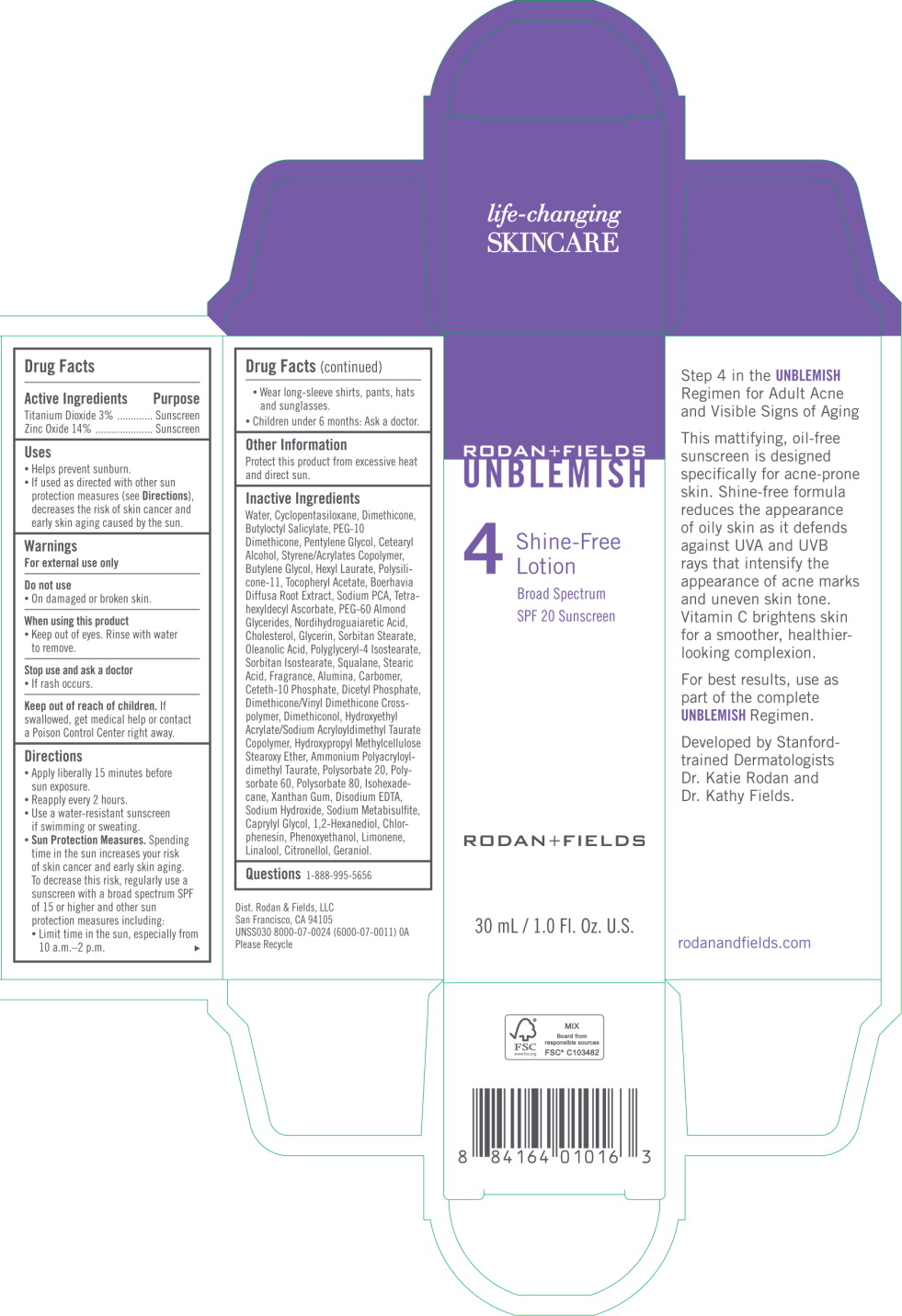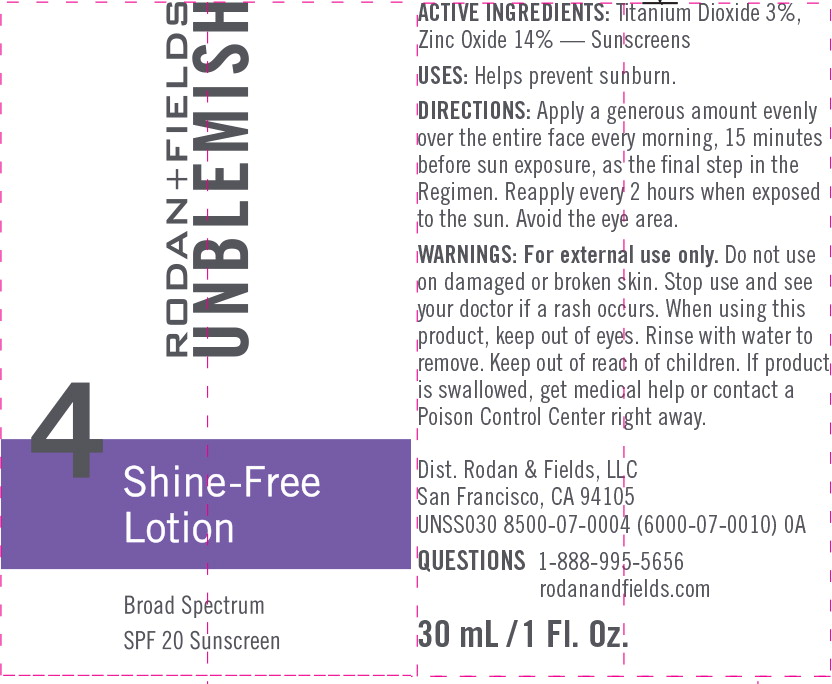 DRUG LABEL: UNBLEMISH Shine Free
NDC: 14222-2130 | Form: LOTION
Manufacturer: Rodan & Fields
Category: otc | Type: HUMAN OTC DRUG LABEL
Date: 20190213

ACTIVE INGREDIENTS: TITANIUM DIOXIDE 0.03 g/1 mL; ZINC OXIDE 0.14 g/1 mL
INACTIVE INGREDIENTS: WATER; CYCLOMETHICONE 5; DIMETHICONE; BUTYLOCTYL SALICYLATE; PEG-10 DIMETHICONE (600 CST); PENTYLENE GLYCOL; CETOSTEARYL ALCOHOL; BUTYLENE GLYCOL; HEXYL LAURATE; .ALPHA.-TOCOPHEROL ACETATE, DL-; 1,2-HEXANEDIOL; ALUMINUM OXIDE; BOERHAVIA DIFFUSA ROOT; CAPRYLYL GLYCOL; CARBOXYPOLYMETHYLENE; CETETH-10 PHOSPHATE; CHLORPHENESIN; CHOLESTEROL; DIHEXADECYL PHOSPHATE; DIMETHICONE/VINYL DIMETHICONE CROSSPOLYMER (SOFT PARTICLE); DIMETHICONOL (600000 CST); EDETATE DISODIUM ANHYDROUS; GLYCERIN; GLYCERYL MONOSTEARATE; ISOHEXADECANE; OLEANOLIC ACID; PEG-100 STEARATE; PEG-60 ALMOND GLYCERIDES; PHENOXYETHANOL; POLYGLYCERYL-4 ISOSTEARATE; POLYSORBATE 20; POLYSORBATE 60; POLYSORBATE 80; SODIUM HYDROXIDE; SODIUM METABISULFITE; SODIUM PYRROLIDONE CARBOXYLATE; SORBITAN ISOSTEARATE; SQUALANE; STEARIC ACID; TETRAHEXYLDECYL ASCORBATE; XANTHAN GUM; LIMONENE, (+)-; LINALOOL, (+/-)-; .BETA.-CITRONELLOL, (R)-; GERANIOL

Drug Facts

Active Ingredients

Titanium Dioxide 3%

Zinc Oxide 14%

Purpose

Sunscreen

Sunscreen

Uses

- Helps prevent sunburn.
- lf used as directed with other sun protection measures (see Directions), decreases the risk of skin cancer and early skin aging caused by the sun.

Warnings

For external use only

Do not use

- On damaged or broken skin.

When using this product

- Keep out of eyes. Rinse with water to remove.

Stop use and ask a doctor

- If rash occurs.

Keep out of reach of children. If swallowed, get medical help or contact a Poison Control Center right away.

Directions

- Apply liberally 15 minutes before sun exposure.
- Reapply every 2 hours.
- Use a water-resistant sunscreen if swimming or sweating.
- Sun Protection Measures. Spending time in the sun increases your risk of skin cancer and early skin aging. To decrease this risk, regularly use a sunscreen with a broad spectrum SPF of 15or higher and other sun protection measures including:
  - Limit time in the sun, especially from 10 a.m.-2 p.m.
  - Wear long-sleeve shirts, pants, hats and sunglasses.
- Children under 6 months: Ask a doctor.

Other Information

Protect this product from excessive heat and direct sun.

Inactive Ingredients

Water,Cyclopentasiloxane,Dimethicone, Butyloctyl Salicylate, PEG-10 Dimethicone, Pentylene Glycol, Cetearyl Alcohol, Styrene/Acrylates Copolymer, Butylene Glycol, Hexyl Laurate, Polysilicone-11, Tocopheryl Acetate, Boerhavia Diffusa Root Extract, Sodium PCA, Tetrahexyldecyl Ascorbate, PEG-60 Almond Glycerides, Nordihydroguaiaretic Acid, Cholesterol, Glycerin, Sorbitan Stearate, Oleanolic Acid, Polyglyceryl-4 lsostearate, Sorbitan lsostearate, Squalane, Stearic Acid, Fragrance, Alumina, Carbomer, Ceteth-10 Phosphate, Dicetyl Phosphate, Dimethicone/Vinyl Dimethicone Crosspolymer, Dimethiconol, Hydroxyethyl Acrylate/Sodium Acryloyldimethyl Taurate Copolymer, Hydroxypropyl Methylcellulose Stearoxy Ether, Ammonium Polyacryloyldimethyl Taurate, Polysorbate 10, Polysorbate 60, Polysorbate 80, lsohexadecane, Xanthan Gum, Disodium EDTA, Sodium Hydroxide, Sodium Metabisulfite, Caprylyl Glycol, 1,2-Hexanediol, Chlorphenesin, Phenoxyethanol, Limonene, Linalool, Citronellol, Geraniol.

Questions

1-888-995-5656

Principal Display Panel - 30 mL Carton Label

RODAN+FIELDS

UNBLEMISH

4 Shine-Free
Lotion

Broad Spectrum

SPF 20 Sunscreen

RODAN+FIELDS

30 mL/1.0 Fl. Oz. U.S.

Principal Display Panel - 30 mL Tube Label

RODAN+FIELDS

UNBLEMISH

4 Shine-Free
Lotion

Broad Spectrum

SPF 20 Sunscreen